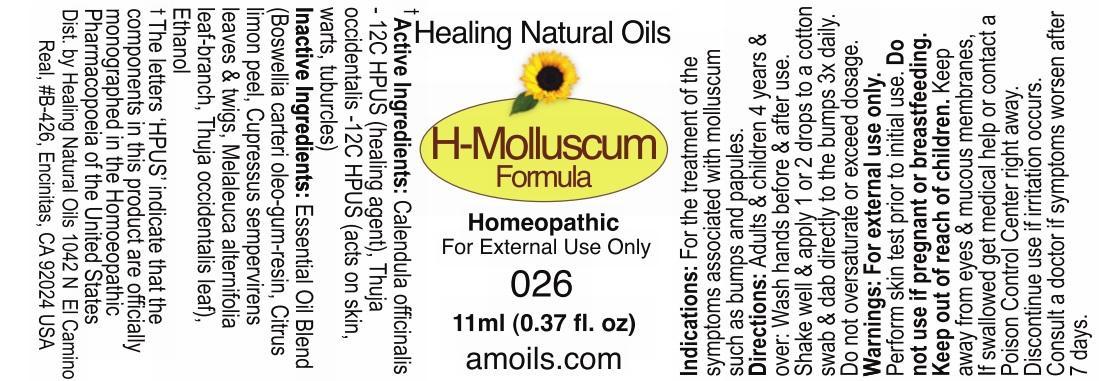 DRUG LABEL: H-Molluscum Formula
NDC: 61077-026 | Form: OIL
Manufacturer: Healing Natural Oils LLC
Category: homeopathic | Type: HUMAN OTC DRUG LABEL
Date: 20241211

ACTIVE INGREDIENTS: CALENDULA OFFICINALIS FLOWERING TOP 12 [hp_C]/11 mL; THUJA OCCIDENTALIS LEAFY TWIG 12 [hp_C]/11 mL
INACTIVE INGREDIENTS: FRANKINCENSE; LEMON PEEL; CUPRESSUS SEMPERVIRENS LEAFY TWIG; MELALEUCA ALTERNIFOLIA LEAF; THUJA OCCIDENTALIS LEAF; ALCOHOL

Active Ingredients:

Calendula officinalis -12C HPUS,
Thuja occidentalis - 12C HPUS

Purpose

Calendula officinalis -12C HPUS (healing agent),
Thuja occidentalis 12C HPUS (acts on skin, warts, tuburcles)
The letters ‘HPUS’ indicate that the components in this product are officially
monographed in the Homoeopathic Pharmacopoeia of the United States

Inactive Ingredients:

Essential Oil Blend (Boswellia carteri oleo-gum-resin, Citrus limon peel, Cupressus sempervirens leaves and twigs, Melaleuca alterniforlia leaf-branch, Thuja occidentalis leaf), Ethanol

Indications:

For the treatment of the symptoms associated with molluscum such as bumps and papules.

Directions:

Adults and children 4 years and over: Wash hands before and after use.
Shake well and apply 1 or 2 drops to a cotton swab and dab to the bumps 3x daily.
Do not oversaturate or exceed dosage.

Warnings:

For external use only.

Perform skin test prior to initial use.

Do not use if pregnant or breastfeeding.

Keep out of reach of children.

OTHER SAFETY INFORMATION

Keep away from eyes and mucous membranes. If swallowed get medical help
or contact a Poison Control Center right away.

Discontinue use if irritation occurs.

ASK DOCTOR

Consult a doctor if symptoms worsen after 7 days.

DESCRIPTION

Dist. by Healing Natural Oils 1042 N El Camino Real,

#B-426, Encinitas, CA 92024 USA

Principal Display Panel

Healing Natural Oils

H-Molluscum
Formula

Homeopathic

For External Use Only

026

11ml (0.37 fl. oz)
amoils.com